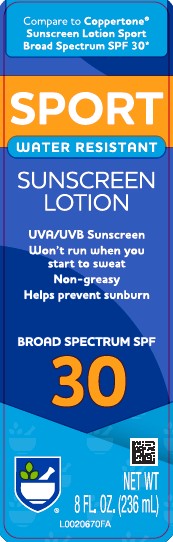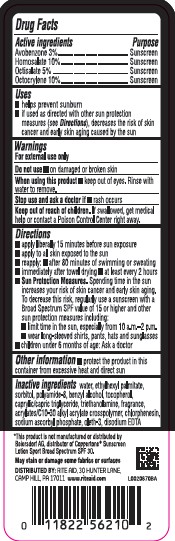 DRUG LABEL: Sunscreen
NDC: 11822-0714 | Form: LOTION
Manufacturer: Rite Aid Corporation
Category: otc | Type: HUMAN OTC DRUG LABEL
Date: 20260130

ACTIVE INGREDIENTS: AVOBENZONE 30.3 mg/1 mL; HOMOSALATE 101 mg/1 mL; OCTISALATE 50.5 mg/1 mL; OCTOCRYLENE 101 mg/1 mL
INACTIVE INGREDIENTS: WATER; ETHYLHEXYL PALMITATE; SORBITOL; POLYAMIDE-8 (4500 MW); BENZYL ALCOHOL; TOCOPHEROL; MEDIUM-CHAIN TRIGLYCERIDES; TROLAMINE; CARBOMER INTERPOLYMER TYPE A (ALLYL SUCROSE CROSSLINKED); CHLORPHENESIN; SODIUM ASCORBYL PHOSPHATE; OLETH-3; EDETATE DISODIUM ANHYDROUS

Rite Aid_Daylogic 714.000/714AA
Sport Sunscreen Lotion SPF 30

Active Ingredients

Avobenzone 3%

Homosalate 10%

Octisalate 5%

Octocrylene 10%

Purpose

Sunscreen

Uses

- helps prevent sunburn
- if used as directed with other sun protections measures (see Directions), decreases the risk of skin cancer and early skin aging caused by the sun

Warnings

For external use only

Do not use

- on damaged or broken skin

When using this product

- keep out of eyes. Rinse with water to remove.

Stop use and ask a doctor if

- rash occurs

Keep out of reach of children.

If swallowed, get medical help or contact a Poison Control Center right away.

Directions

- apply liberally 15 minutes before sun exposure
- apply to all skin exposed to the sun
- reapply:
- after 80 minutes of swimming or sweating
- immediately after towel drying
- at least every 2 hours
- Sun Protection Measures.Spending time in the sun increases your risk of skin cancer and early skin aging. To decrease this risk, regularly use a sunscreen with a Broad Spectrum SPF value of 15 or higher and other sun protection measures including:
- limit time in the sun, especially from 10 a.m.–2 p.m.
- wear long-sleeved shirts, pants, hats and sunglasses
- children under 6 months of age: Ask a doctor

Other Information

- Protect the product in this container from excessive heat and direct sun

Inactive ingredients

water, ethylhexyl palmitate, sorbitol, polyamide-8, benzyl alcohol, tocopherol, caprylic/capric triglyceride, triethanolamine, fragrance, acrylates/C10-30 alkyl acrylate crosspolymer, chlorphenesin, sodium ascorbyl phosphate, oleth-3, disodium EDTA

Disclaimers

*This product is not manufactured or distributed by Beiersdorf AG, distributor of CoppertoneSunscreen Lotion Sport Broad Spectrum SPF 30.

May stain or damage some fabrics or surfaces.

ADVERSE REACTION

DISTRIBUTED BY: RITE AID, 30 HUNTER LANE

CAMP HILL, PA 17011 www.riteaid.com

principal display panel

Compare to Coppertone®Sunscreen Lotion Sport Broad Spectrum SPF 30*

SPORT

WATER RESISTANT

SUNSCREEN LOTION

UVA/UVB Sunscreen

Won't run when you start to sweat

Non-greasy

Helps prevent sunburn

BROAD SPECTRUM SPF 30

NET WT 8 FL. OZ. (236 mL)